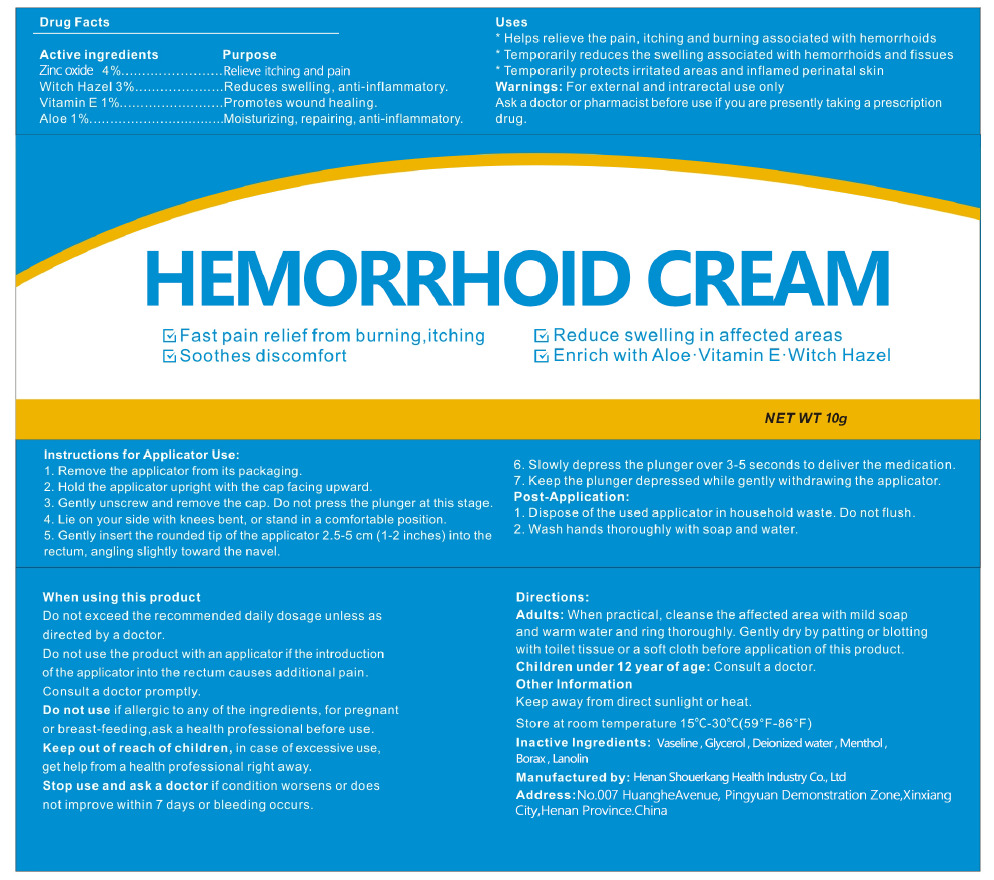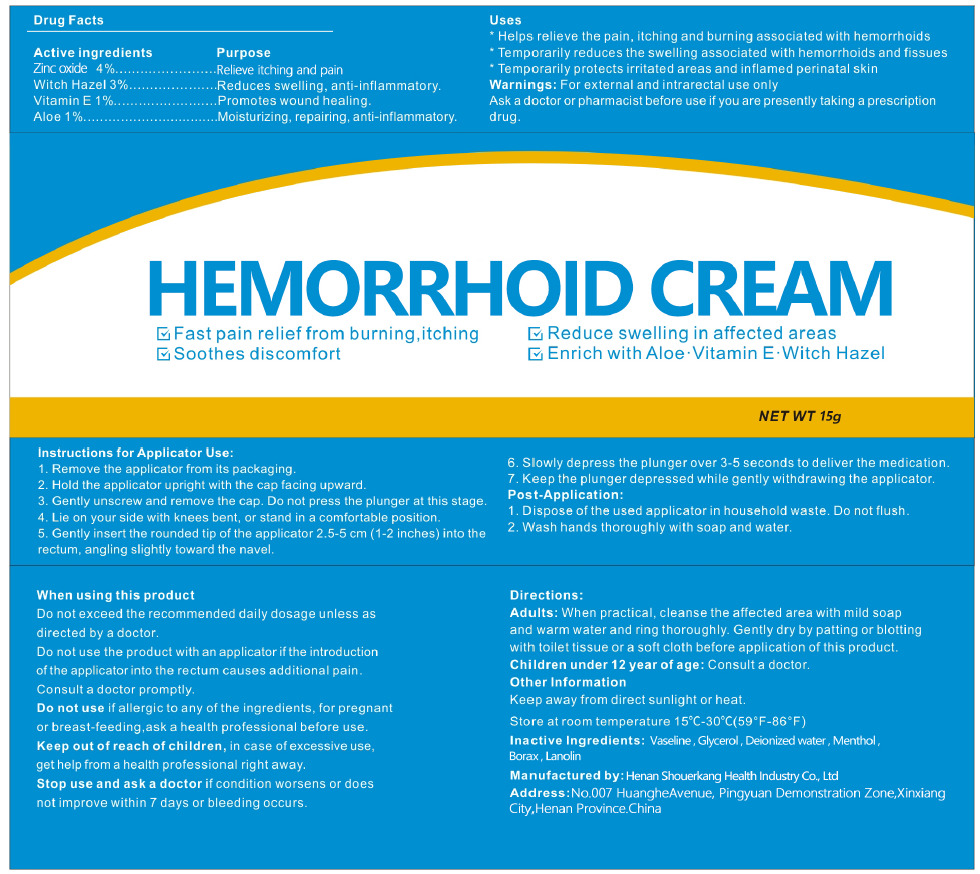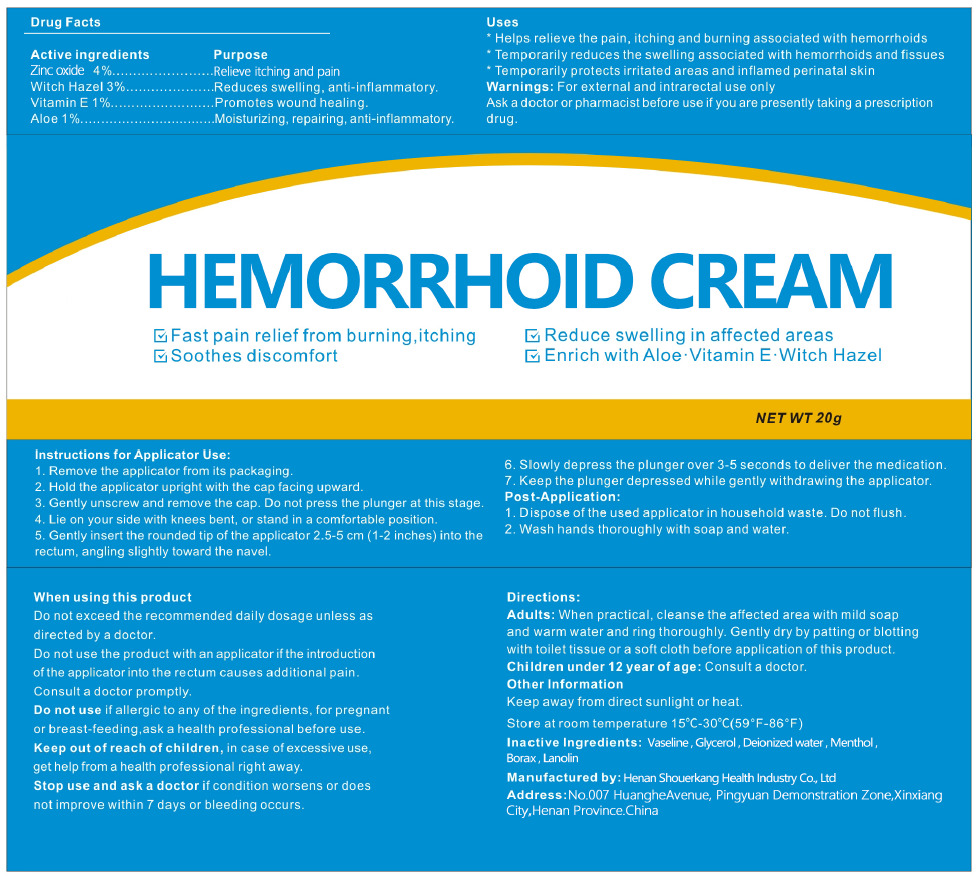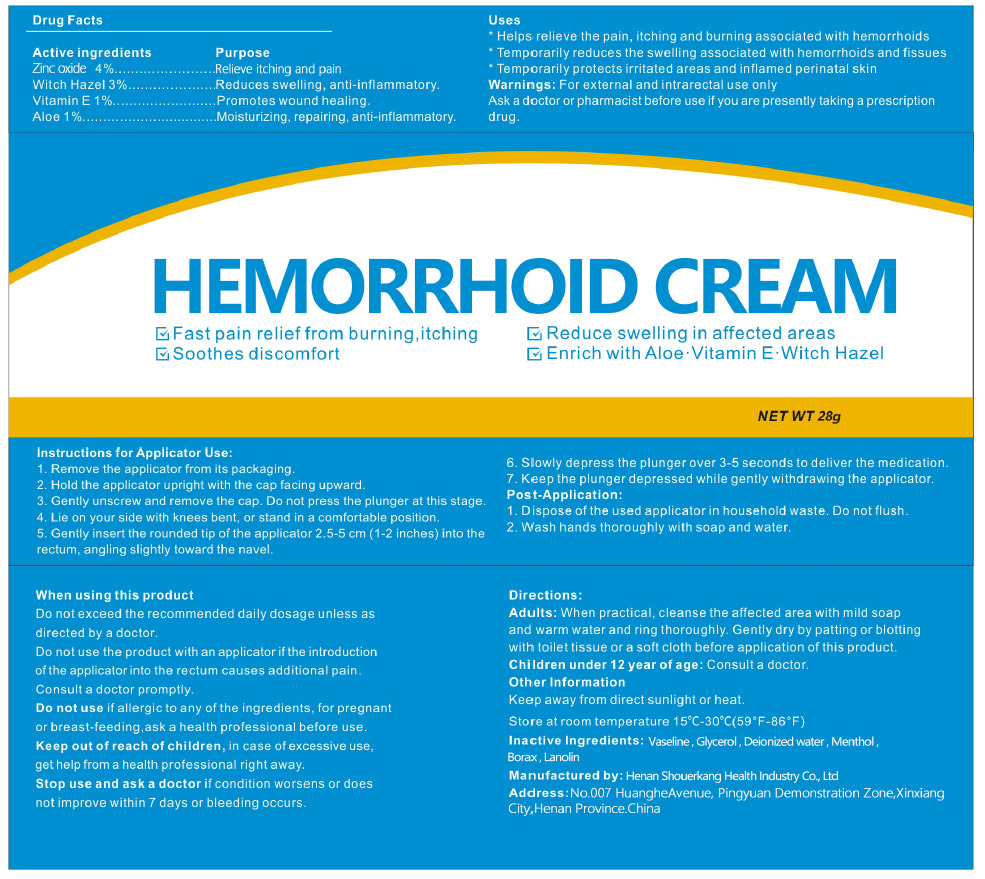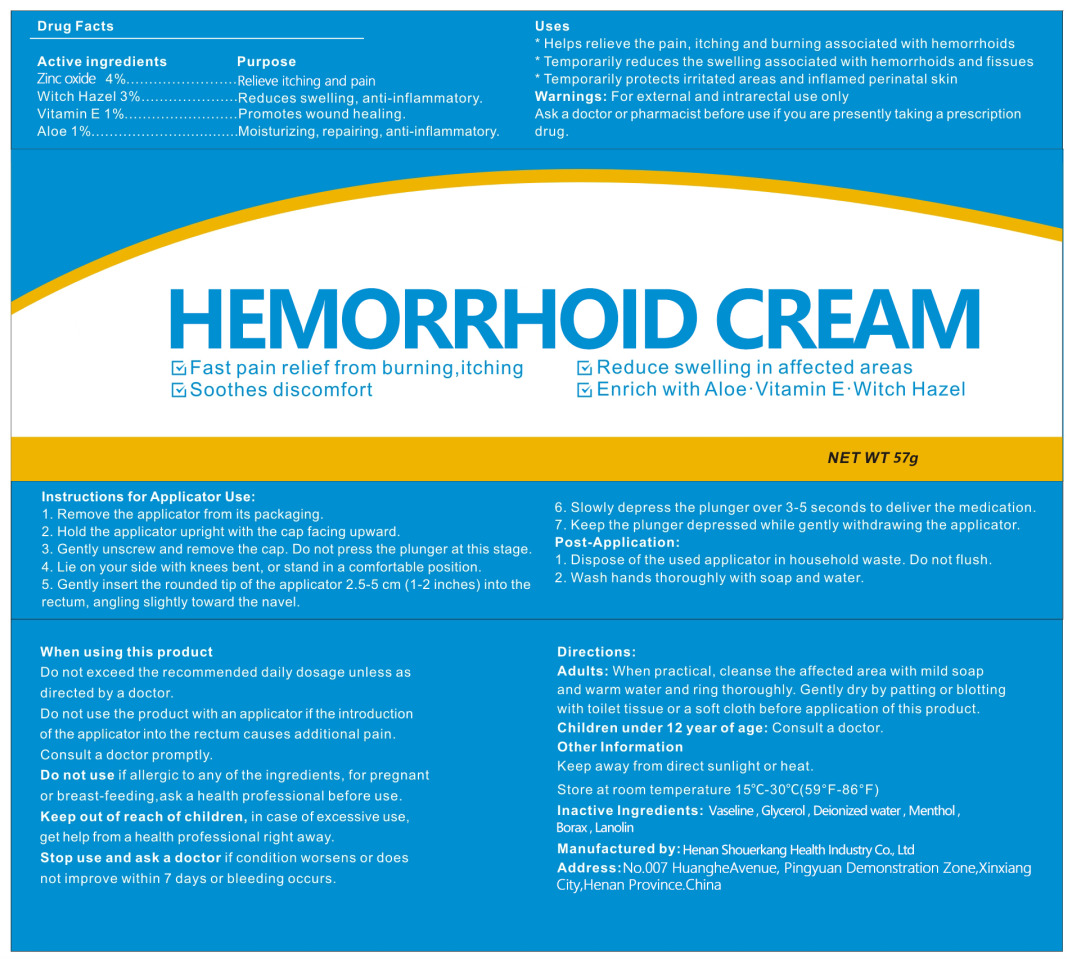 DRUG LABEL: Hemorrhoid Cream
NDC: 85056-003 | Form: CREAM
Manufacturer: Henan Shouerkang Health Industry Co., Ltd
Category: otc | Type: HUMAN OTC DRUG LABEL
Date: 20250707

ACTIVE INGREDIENTS: ZINC OXIDE 10 g/100 g; .ALPHA.-TOCOPHEROL 1 g/100 g; ALOE 1 g/100 g; WITCH HAZEL 3 g/100 g
INACTIVE INGREDIENTS: PETROLATUM; GLYCERIN; WATER; MENTHOL; SODIUM BORATE; LANOLIN

85056-003

Active Ingredient(s)

Zinc oxide 4%
Witch Hazel 3%
Vitamin E 1 %
Aloe 1%

Purpose

Relieve itching and pain
Reduces swelling, anti-inflammatory.
Promotes wound healing.
Moisturizing, repairing, anti-inflammatory.

Use

1.Helps relieve the pain, itching and burning associated with hemorrhoids
2.Temporarily reduces the swelling associated with hemorrhoids and fissues
3.Temporarily protects irritated areas and inflamed perinatal skin

Warnings

Warnings: For external and intrarectal use only
Ask a doctor or pharmacist before use if you are presently taking a prescription
drug.

Do not use

1. Do not use the product with an applicator if the introduction of the applicator into the rectum causes additional pain.
Consult a doctor promptly.
2. Do not use if allergic to any of the ingredients, for pregnant or breast-feeding,ask a health professional before use.

WHEN USING

Do not exceed the recommended daily dosage unless as directed by a doctor.

Stop use and ask a doctor if condition worsens or does
not improve within 7 days or bleeding occurs.

Keep out of reach of children, in case of excessive use, get help from a health professional right away.

Directions

Adults: When practical, cleanse the affected area with mild soap
and warm water and ring thoroughly. Gently dry by patting or blotting
with toilet tissue or a soft cloth before application of this product.
Children under12 year of age: Consult a doctor.

Other information

Keep away from direct sunlight or heat.
Store at room temperature 15°C-30°C(59°F-86°F)

Inactive ingredients

Vaseline, Glycerol ，Deionized water，Menthol，Borax，Lanolin